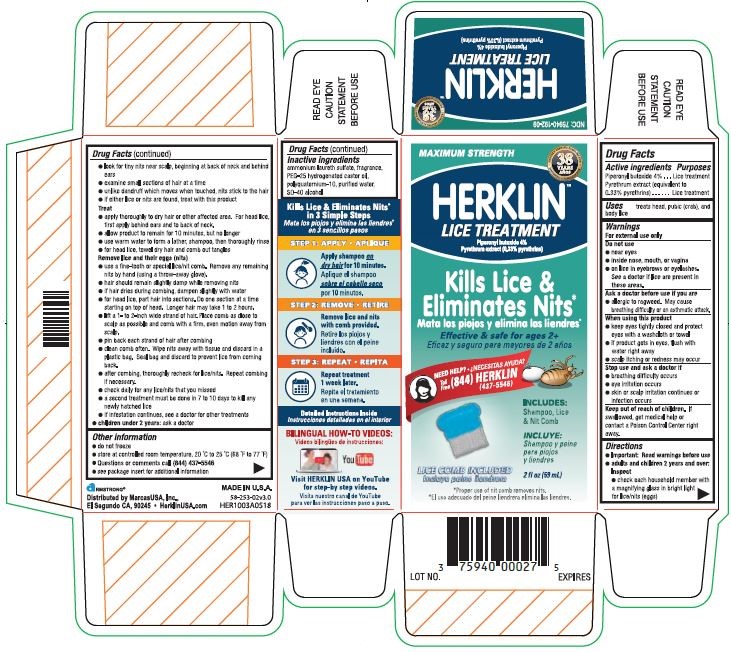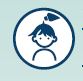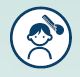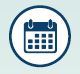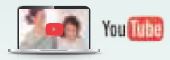 DRUG LABEL: Herklin Lice Treatment
NDC: 75940-192 | Form: SHAMPOO
Manufacturer: MarcasUSA LLC
Category: otc | Type: HUMAN OTC DRUG LABEL
Date: 20180716

ACTIVE INGREDIENTS: PIPERONYL BUTOXIDE 4 g/100 mL; PYRETHRUM EXTRACT 0.33 g/100 mL
INACTIVE INGREDIENTS: PEG-25 HYDROGENATED CASTOR OIL; POLYQUATERNIUM-10 (125 MPA.S AT 2%); ALCOHOL; WATER

Herklin Lice Treatment

Drug Facts

Active Ingredients

Piperonyl butoxide 4%.........................................................................Lice Treatment

Pyrethrum extract (equivalent to 0.33 % pyrethrins.................................Lice Treatment

Inactive Ingredients

ammonium laureth sulfate, fragrance, PEG-25 hydrogenated castor oil, polyquaternium-10, purified water, SD-40 alcohol

Purpose

Treatment head, pubic (crab), and body lice

Uses

Uses treats head lice, pubic (crab) lice, and body lice

Warnings

For external use only. Do not use

- near eyes
- inside nose, mouth or vagina
- on lice in eyebrows or eyelashes. See a doctor if lice are present in these areas.

Ask a doctor before us if you are

- allergic to ragweed, May cause breathing difficulty or an asthmatic attack.

When using this product

- keep eyes tightly closed and protect eyes with a washcloth or towel
- if product gets in eyes, flush with water right away
- scalp itching or redness may occur.

Stop use and ask doctor if

- breathing difficulty occurs
- eye irrirtation occurs
- skin or scalp irritation continues or infection occurs

Keep out of reach of children

If swallowed, get medical help or contact a Poison Control Center right away.

Directions

- Important: Read warnings before use.
- adults and children 2 years and over: Inspect
- check each household member with a magnifying glass in bright light for lice/nits (eggs)
- look for tiny nits near scalp, beginin at back of neck and behind ears
- examine small sections of hair at a time
- unlike dandruff which moves when touched, nits stick to the hair
- if either lice or nits are found, treat with this product

Treat

- apply thoroughly to dry hair or other affected area. For head lice, first apply behind ears and to back of neck.
- allow product to remain for 10 minutes, but no longer
- use warm water to form a lather, shampoo, then thoroughly rinse
- for head lice, towel dry hair and comb out tangles.

Remove lice and their eggs (nits)

- use a fine-tooth or special lice/nit comb. Remove any remaining nits by hand (using a throw-away glove.)
- hair should remain slightly damp while removing nits
- if hair dries during combing dampen slightly with water
- for head lice, part hair into sections. Do one section at a time starting on top of head. Longer hair may take 1 to 2 hours.
- life a 1- to 2- inch wide strand of hair. Place comb as close to scalp as possible and comb with a firm, even motion away from scalp.
- Pin back each strand of hair after combing
- clean comb often. Wipe nits away with tissue and discard in a plastic bag. Seal bag and discard to prevent lice froom coming back.
- after combing, thoroughly recheck for lice/nits. Repeat combing if necessary.
- a second treatment must be done in 7 to 10 days to kill any newly hatched lice
- If infestation continues, see a doctor for other treatments.
- children under 2 years: aska doctor

Other Information

- do not freeze
- store at controlled room temperature, 20 °C to 25 ° C (68 ºF to 77 ºF)
- Questions or comments call (844) 437-5546
- see package insert for additional information

Consumer Information

Kills Lice & Eliminates Nits in 3 simple steps

STEP 1: APPLY • APLIQUE

Apply shampoo on dry hair for 10 minutes.

STEP 2: REMOVE • RETIRE

Remove lice and nits with comb provided.

STEP 3: REPEAT • REPITA

Repeat treatment 1 week later.

Detailed Instructions Inside

BILINGUAL HOW-TO VIDEOS

Visit HERKLINE USA on YouTube for step-by-step videos.

Distributed by MarcasUSA, Inc.,

El Segundo, CA 90245 • HerklineUSA.com

Made in U.S.A

58-253-02v3.0

Principal Display Panel - 236 mL Bottle Carton

MAXIMUM STRENGTH

• PROUDLY SERVING FAMILIES FOR •
38
YEARS

HERKLIN®
LICE TREATMENT

Piperonyl butoxide 4%
Pyrethrum extract (0.33% pyrethrins)

Kills Lice &
Eliminates Nits*

Effective & safe for ages 2+

NEED HELP? •
Toll
Free
(844) HERKLIN
(437-5546)

INCLUDES:
Shampoo, Lice
& Nit Comb

LICE COMB INCLUDED

2 fl oz (59 mL)

*Proper use of nit comb removes nits